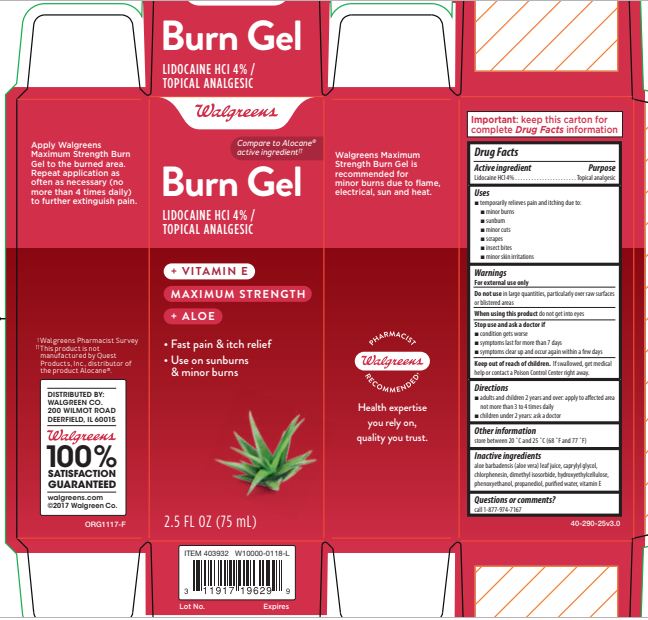 DRUG LABEL: Walgreens Burn relief
NDC: 0363-0290 | Form: GEL
Manufacturer: Walgreens
Category: otc | Type: HUMAN OTC DRUG LABEL
Date: 20190509

ACTIVE INGREDIENTS: LIDOCAINE HYDROCHLORIDE 4 g/100 g
INACTIVE INGREDIENTS: HYDROXYETHYL CELLULOSE (100 MPA.S AT 2%); PHENOXYETHANOL; CAPRYLYL GLYCOL; ALOE VERA LEAF; PROPANEDIOL; DIMETHYL ISOSORBIDE; WATER; CHLORPHENESIN; .ALPHA.-TOCOPHEROL ACETATE

Walgreens Lidocaine Hydrochloride Burn Gel

Active ingredient

Lidocaine HCl 4%......................................................................................................................... Topical analgesic

Uses

Temporarily relieves pain and itching due to: minor burns, sunburn, minor cuts, scrapes, insect bites, minor skin irritations

Warnings

For external use only

Do Not Use

In large quantities, particularly over raw surfaces or blistered areas

When Using This Product

Do not get into eyes

Stop use and ask doctor if

condition gets worse

symptoms last for more than 7 days

symptoms clear up and occur again within a few days

Keep out of reach of children

If swallowed, get medical help or contact a Poison Control Center right away.

Directions

adults and children 2 years and over: apply to affected area not more than 3 to 4 times daily

children under 2 years: ask a doctor

Purpose

Burns Relief topical analgesic

Other Information

Store between 20 °C and 25 °C (68 °F and 77 °F)

Inactive Ingredients

Aloe barbadensis (aloe vera) leaf juice, caprylyl glycol, chlorphensin, dimethyl isosorbide, hydroxyethyl cellulose, phenoxyethanol, propanediol, purified water, vitamin E

Prncipal Display Panel

Walgreens

Burn Gel LIDOCAINE HCl 4%

Compare to Alocane® active ingredient††

TOPICAL ANALGESIC

+ Vitamin E

Maximum Strength

+ Aloe

• Fast pain & itch relief

• Use on sunburns & minor burns